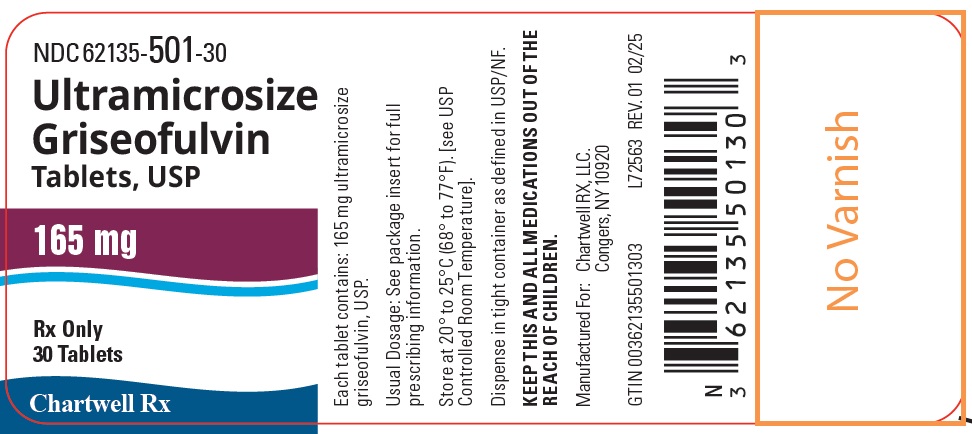 DRUG LABEL: ULTRAMICROSIZE GRISEOFULVIN
NDC: 62135-501 | Form: TABLET
Manufacturer: Chartwell RX, LLC
Category: prescription | Type: HUMAN PRESCRIPTION DRUG LABEL
Date: 20250220

ACTIVE INGREDIENTS: GRISEOFULVIN 165 mg/1 1
INACTIVE INGREDIENTS: STARCH, CORN; ANHYDROUS LACTOSE; MAGNESIUM STEARATE; POLYETHYLENE GLYCOL 8000; SODIUM LAURYL SULFATE

Ultramicrosize Griseofulvin Tablets, USP

DESCRIPTION

Ultramicrosize Griseofulvin Tablets, USP contain ultramicrosize crystals of griseofulvin, an antibiotic derived from a species of Penicillium. Griseofulvin crystals are partly dissolved in polyethylene glycol 8000 and partly dispersed throughout the label matrix.

Each Ultramicrosize Griseofulvin Tablet, USP contains 165 mg ultramicrosize griseofulvin, USP.

The inactive ingredients for Ultramicrosize Griseofulvin Tablets, USP include: corn starch, lactose anhydrous, magnesium stearate, polyethylene glycol 8000, and sodium lauryl sulfate.

ACTIONS MicrobiologyGriseofulvin is fungistatic with in vitroactivity against various species of Microsporum, Epidermophyton, and Trichophyton. It has no effect on bacteria or on other genera of fungi.

Human PharmacologyFollowing oral administration, griseofulvin is deposited in the keratin precursor cells and has a greater affinity for diseased tissue. The drug is tightly bound to the new keratin which becomes highly resistant to fungal invasions.

The efficiency of gastrointestinal absorption of ultramicrocrystalline griseofulvin is approximately one and one-half times that of the conventional microsize griseofulvin. This factor permits the oral intake of two-thirds as much ultramicrocrystalline griseofulvin as the microsize form. However, there is currently no evidence that this lower dose confers any significant clinical differences with regard to safety and/or efficacy.

INDICATIONS

Ultramicrosize griseofulvin tablets are indicated for the treatment of ringworm infections of the skin, hair, and nails, namely: tinea corporis, tinea pedis, tinea cruris, tinea barbae, tinea capitis, tinea unguium (onychomycosis) when caused by one or more of the following genera of fungi: Trichophyton rubrum, Trichophyton tonsurans, Trichophyton mentagrophytes, Trichophyton interdigitale, Trichophyton verrucosum, Trichophyton megninii, Trichophyton gallinae, Trichophyton crateriforme, Trichophyton sulphureum, Trichophyton schoenieinii, Microsporum audouini, Microsporum canis, Microsporum gypseum, and Epidermophyton floccosum.

Note: Prior to therapy, the type of fungi responsible for the infection should be identified.

The use of this drug is not justified in minor or trivial infections which will respond to topical agents alone.

Griseofulvin is not effective in the following: bacterial infections, candidiasis (moniliasis), histoplasmosis, actinomycosis, sporotrichosis, chromoblastomycosis, coccidioidomycosis, North American blastomycosis, cryptococcosis (torulosis), tinea versicolor, and nocardiosis.

CONTRAINDICATIONS

This drug is contraindicated in patients with porphyria, hepatocellular failure, and in individuals with a history of hypersensitivity to griseofulvin.

Rare cases of conjoined twins have been reported in patients taking griseofulvin during the first trimester of pregnancy. Griseofulvin should not be prescribed to pregnant patients or to women contemplating pregnancy.

WARNINGS

Prophylactic Usage:Safety and efficacy of griseofulvin for prophylaxis of fungal infections have not been established.

Since griseofulvin has demonstrated harmful effects in vitroon the genotype in bacteria, plants, and fungi, males should wait at least 6 months after completing griseofulvin therapy before fathering a child. Females should avoid risk of pregnancy while receiving griseofulvin therapy.

Animal Toxicology: Chronic feeding of griseofulvin, at levels ranging from 0.5-2.5% of the diet, resulted in the development of liver tumors in several strains of mice, particularly in males. Smaller particle sizes result in an enhanced effect. Lower oral dosage levels have not been tested. Subcutaneous administration of relatively small doses of griseofulvin once a week during the first 3 weeks of life has also been reported to induce hepatomata in mice. Thyroid tumors, mostly adenomas but some carcinomas, have been reported in male rats receiving griseofulvin at levels of 2.0%, 1.0%, and 0.2% of the diet, and in female rats receiving the two higher dose levels. Although studies in other animal species have not yielded evidence of tumorigenicity, these studies were not of adequate design to form a basis for conclusions in this regard.

In subacute toxicity studies, orally administered griseofulvin produced hepatocellular necrosis in mice, but this has not been seen in other species. Disturbances in porphyrin metabolism have been reported in griseofulvin-treated laboratory animals. Griseofulvin has been reported to have a colchicine-like effect on mitosis and cocarcinogenicity with methylcholanthrene in cutaneous tumor induction in laboratory animals.

Griseofulvin interferes with chromosomal distribution during cell division, causing aneuploidy in plant and mammalian cells. These effects have been demonstrated in vitroat concentrations that may be achieved in the serum with the recommended therapeutic dosage.

Usage in Pregnancy:Griseofulvin should not be prescribed to pregnant patients or to women contemplating pregnancy (see CONTRAINDICATIONS).

Animal Reproduction Studies:It has been reported in the literature that griseofulvin was found to be embryotoxic and teratogenic on oral administration to pregnant rats. Pups with abnormalities have been reported in the litters of a few bitches treated with griseofulvin.

Suppression of spermatogenesis has been reported to occur in rats, but investigation in man failed to confirm this.

PRECAUTIONS

Patients on prolonged therapy with any potent medication should be under close observation. Periodic monitoring of organ system function, including renal, hepatic, and hematopoietic, should be done.

Since griseofulvin is derived from species of Penicillium, the possibility of cross-sensitivity with penicillin exists; however, known penicillin-sensitive patients have been treated without difficulty.

Since a photosensitivity reaction is occasionally associated with griseofulvin therapy, patients should be warned to avoid exposure to intense natural or artificial sunlight.

Lupus erythematosus or lupus-like syndromes, or exacerbation of existing lupus, have been reported in patients receiving griseofulvin.

Drug Interactions:Griseofulvin decreases the activity of warfarin-type anticoagulants so that patients receiving these drugs concomitantly may require dosage adjustment of the anticoagulant during and after griseofulvin therapy.

Barbiturates usually depress griseofulvin activity, and concomitant administration may require a dosage adjustment of the antifungal agent.

The effects of alcohol may be potentiated by griseofulvin, producing such effects as tachycardia and flush.

Griseofulvin may potentiate an increase in hepatic enzymes that metabolize estrogens at an increased rate, including the estrogen component of oral contraceptives, thereby causing possible decreased contraceptive effects and menstrual irregularities.

ADVERSE REACTIONS

When adverse reactions occur, they are most commonly of the hypersensitivity type, such as skin rashes and urticaria, and rarely, angioneurotic edema and epidermal necrolysis (Lyell’s syndrome), and may necessitate withdrawal of therapy and appropriate countermeasures. Paresthesias of the hands and feet have been reported rarely after extended therapy. Other side effects reported occasionally are oral thrush, nausea, vomiting, epigastric distress, diarrhea, headache, fatigue, dizziness, insomnia, mental confusion, and impairment of performance of routine activities.

Proteinuria, nephrosis, leukopenia, hepatic toxicity, GI bleeding, and menstrual irregularities have been reported rarely. Administration of the drug should be discontinued if granulocytopenia occurs.

When rare, serious reactions occur with griseofulvin, they are usually associated with high dosages, long periods of therapy, or both.

DOSAGE AND ADMINISTRATION

Accurate diagnosis of the infecting organism is essential. Identification should be made either by direct microscopic examination of a mounting of infected tissue in a solution of potassium hydroxide or by culture on an appropriate medium.

Medication must be continued until the infecting organism is completely eradicated as indicated by appropriate clinical or laboratory examination. Representative treatment periods are tinea capitis, 4 to 6 weeks; tinea corporis, 2 to 4 weeks; tinea pedis, 4 to 8 weeks; tinea unguium – depending on rate of growth – fingernails, at least 4 months; toenails, at least 6 months.

General measures in regard to hygiene should be observed to control sources of infection or reinfection. Concomitant use of appropriate topical agents is usually required, particularly in treatment of tinea pedis. In some forms of athlete’s foot, yeasts and bacteria may be involved as well as fungi. Griseofulvin will not eradicate the bacterial or monilial infection.

Adults:Daily administration of 330 mg (as a single dose or in divided amounts) will give a satisfactory response in most patients with tinea corporis, tinea cruris, and tinea capitis. For those fungus infections more difficult to eradicate, such as tinea pedis and tinea unguium, a divided daily dosage of 660 mg is recommended.

Children:Approximately 3.3 mg per pound of body weight per day is an effective dose for most children. On this basis, the following dosage schedule is suggested: Children weighing 30 to 50 pounds- 82.5 mg to 165 mg daily. Children weighing over 50 pounds – 165 mg to 330 mg daily.

Children 2 years of age and younger – dosage has not been established.

Clinical experience with griseofulvin in children with tinea capitis indicates that a single daily dose is effective. Clinical relapse will occur if the medication is not continued until the infecting organism is eradicated.

HOW SUPPLIED

Ultramicrosize Griseofulvin Tablets, USP 165 mg, off-white, oval shaped, scored tablets debossed with “ C” bisect “ E” on one side and “ 269” on the other side; bottle of 30 (NDC 62135-501-30).

Store at 20° to 25°C (68° to 77°F). [see USP Controlled Room Temperature].

Manufactured for:

Chartwell RX, LLC.

Congers, NY 10920

L72564

Rev. 02/2025

PRINCIPAL DISPLAY PANEL

Ultramicrosize Griseofulvin Tablets, USP 165 mg- NDC 62135-501-30 - 30s Tabs Bottle Label